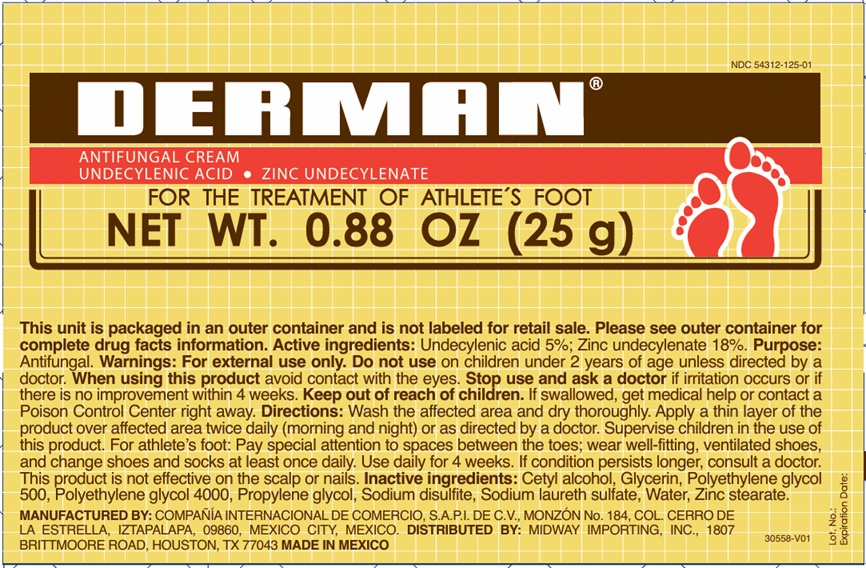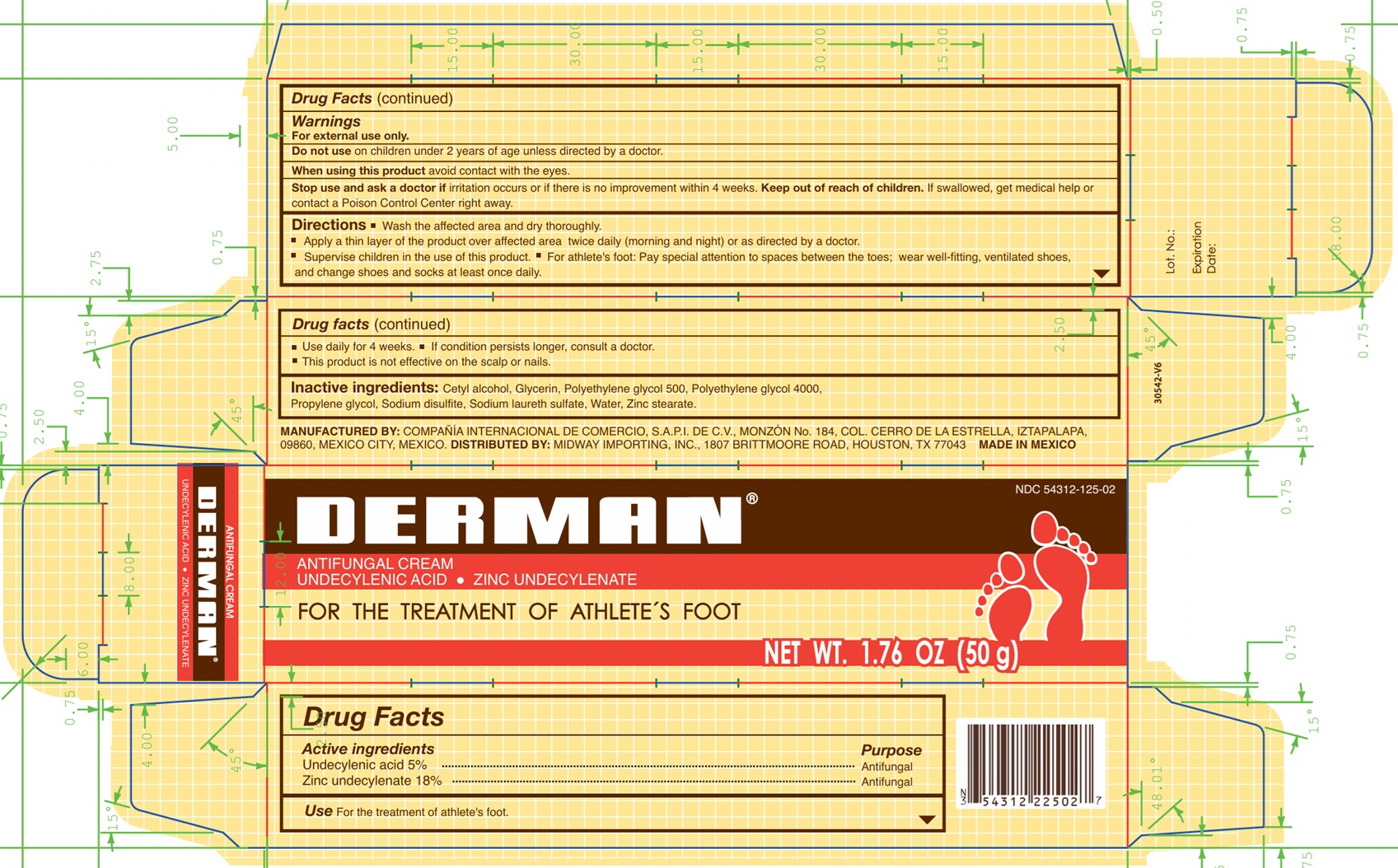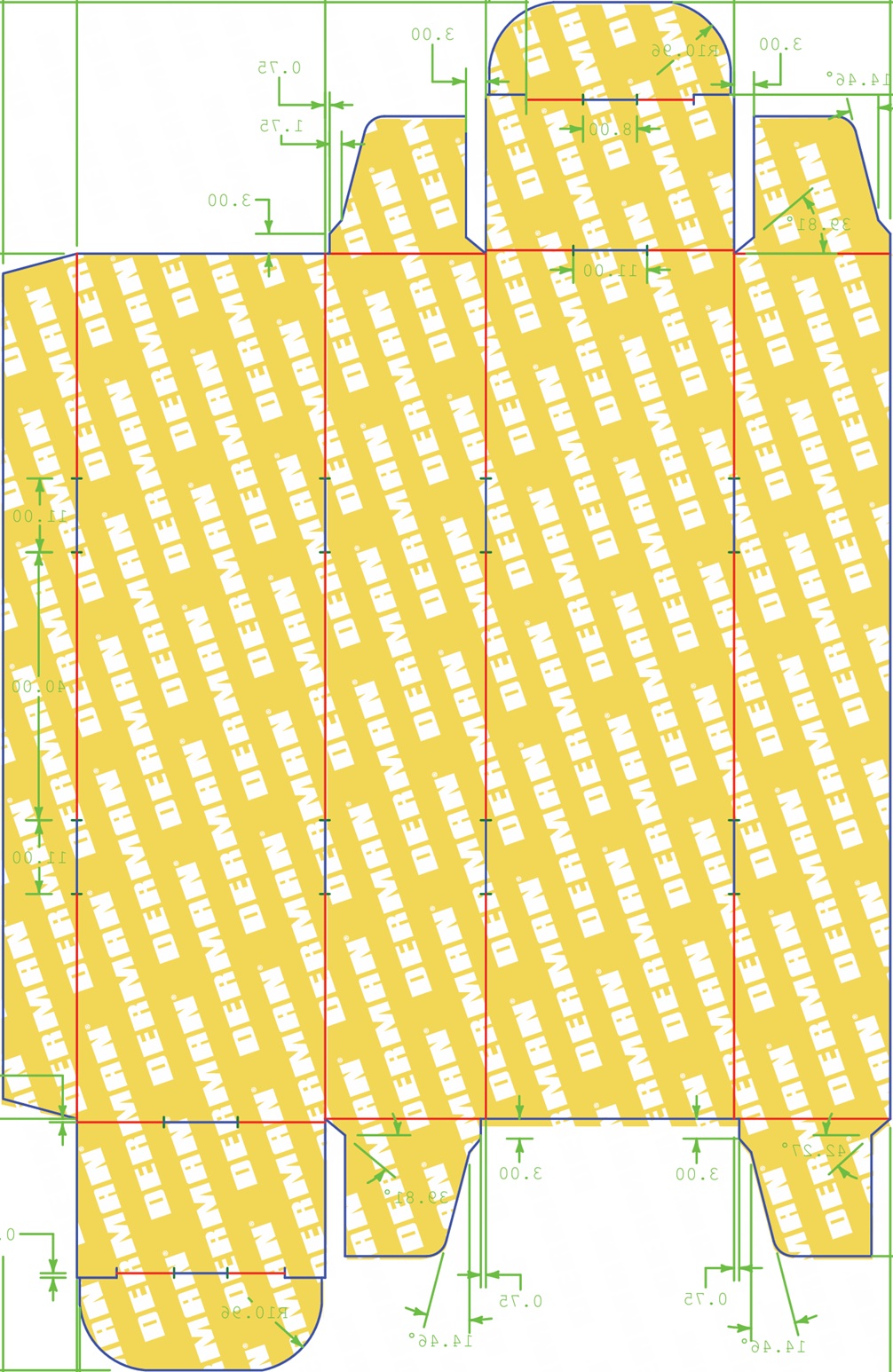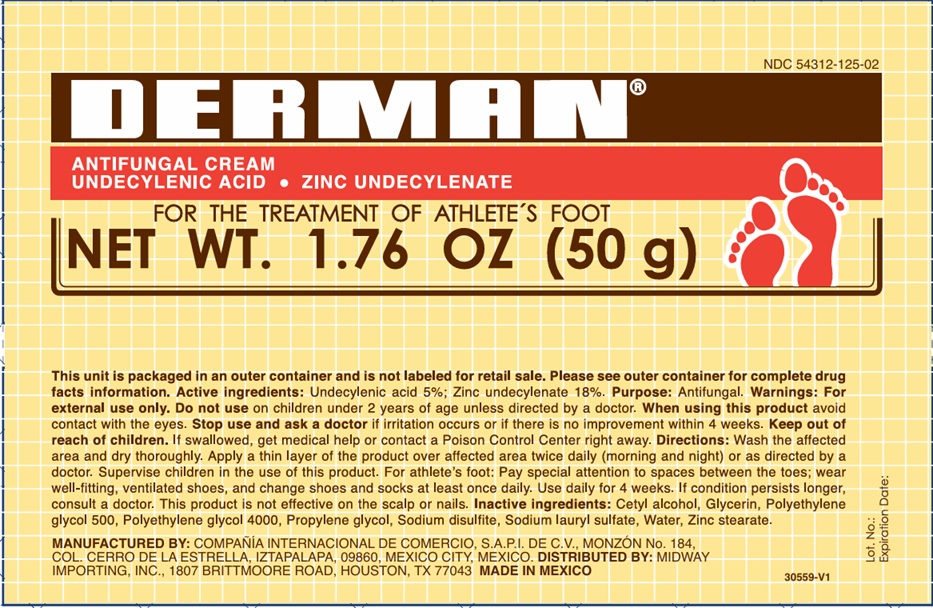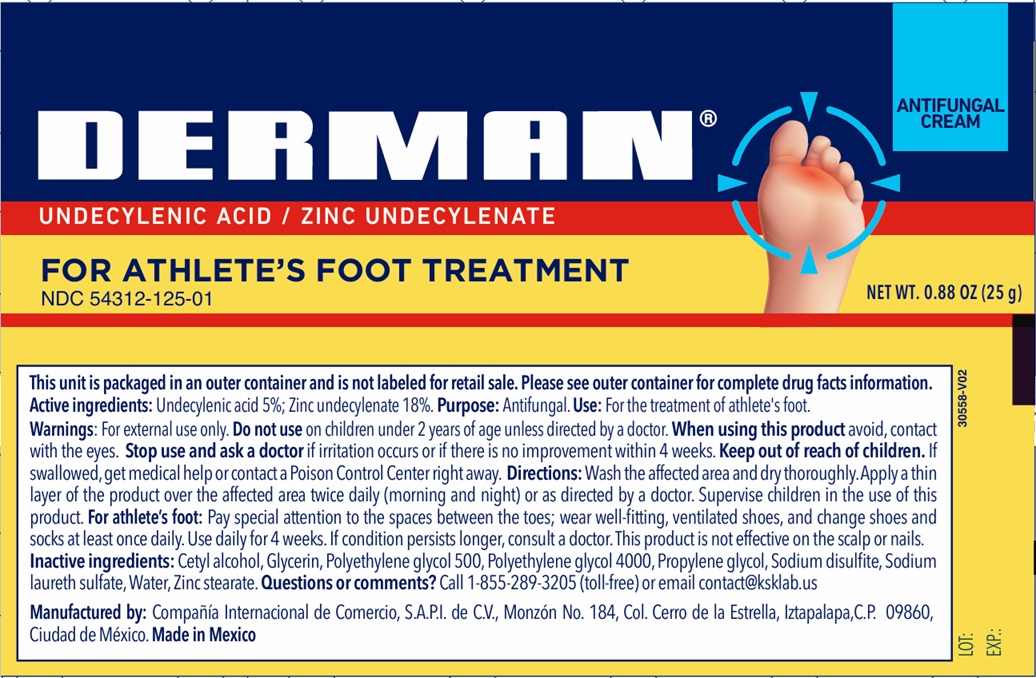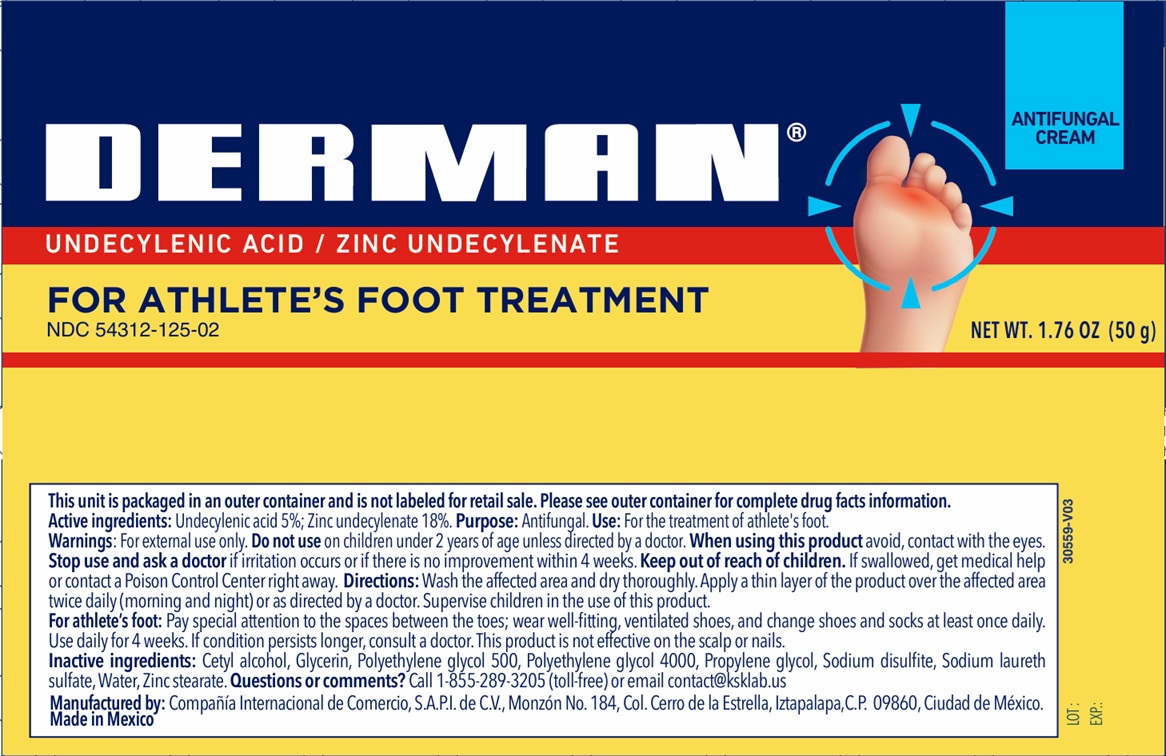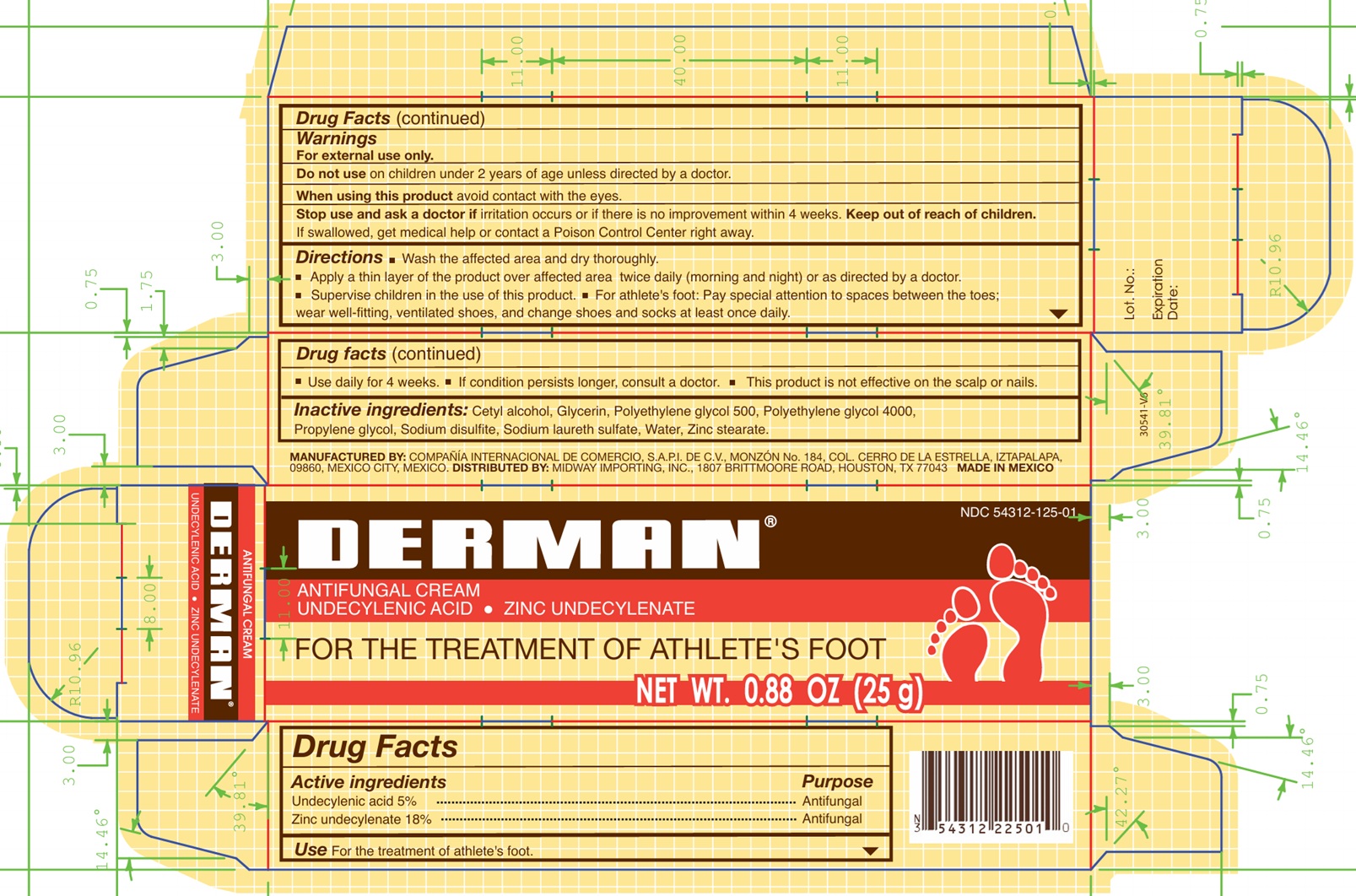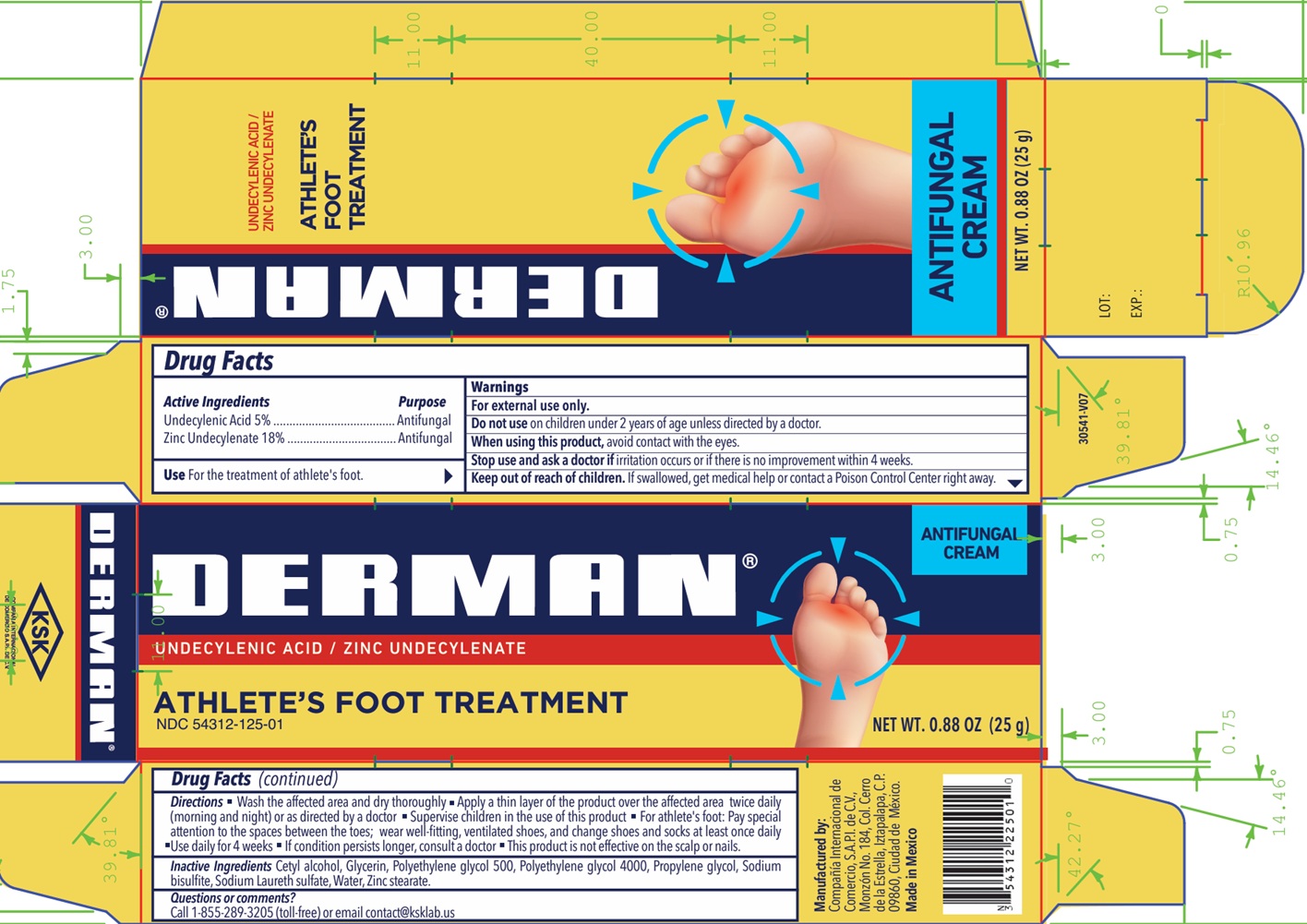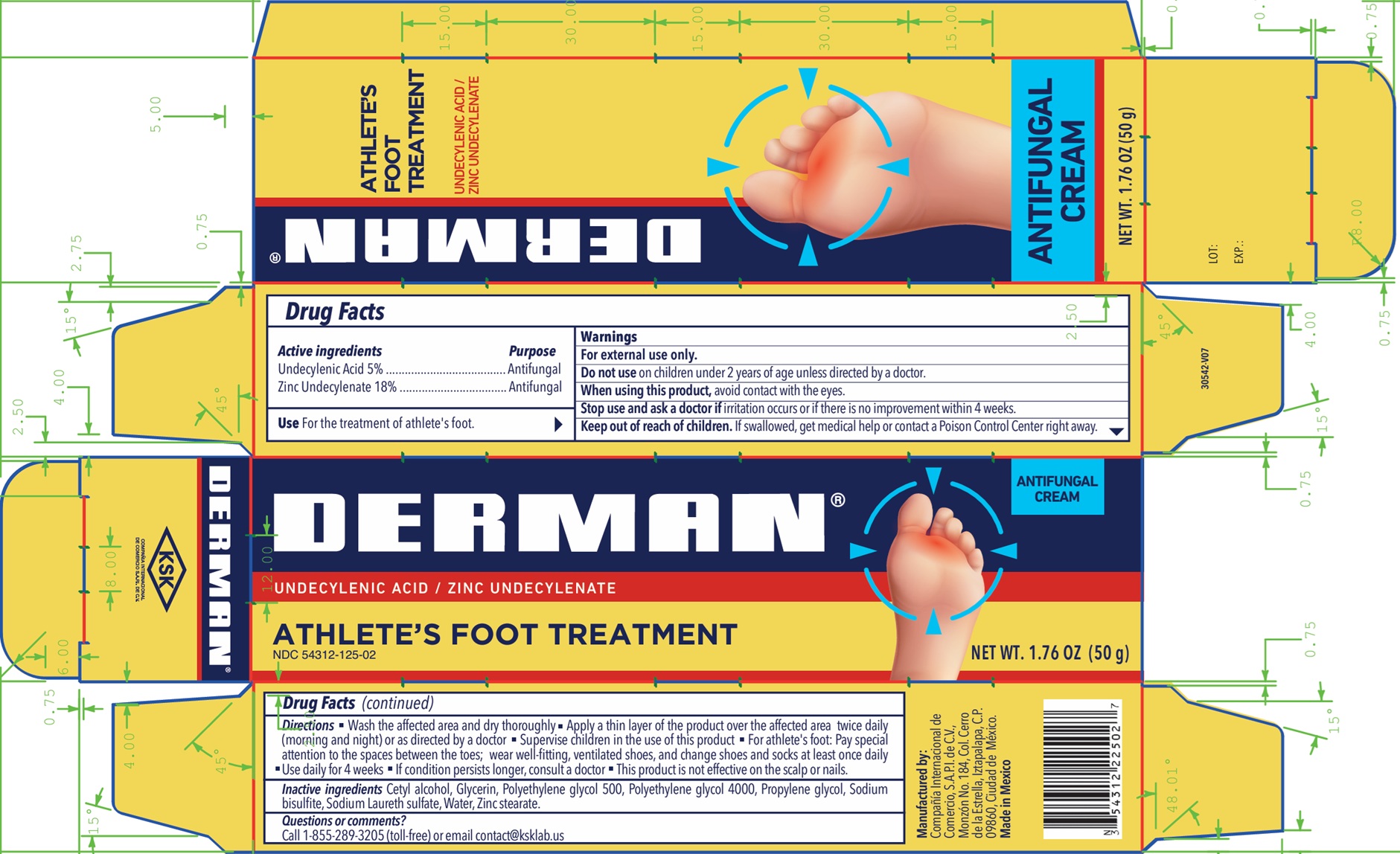 DRUG LABEL: Derman Antifungal
NDC: 54312-125 | Form: CREAM
Manufacturer: Compania Internacional de Comercio, S.A.P.I de C.V.
Category: otc | Type: HUMAN OTC DRUG LABEL
Date: 20251119

ACTIVE INGREDIENTS: UNDECYLENIC ACID 5 g/100 g; ZINC UNDECYLENATE 18 g/100 g
INACTIVE INGREDIENTS: GLYCERIN; POLYETHYLENE GLYCOL 500; POLYETHYLENE GLYCOL 4000; PROPYLENE GLYCOL; CETYL ALCOHOL; SODIUM BISULFITE; SODIUM LAURETH SULFATE; WATER; ZINC STEARATE

Derman Antifungal

Active Ingredients.

Zinc undecylenate 18%

Undecylenic acid 5%

Purpose

Antifungal

Uses

For the treatment of athlete´s foot.

Warnings

For external use only

Do not use

on children under 2 years of age, unless directed by a doctor.

When using this product

Avoid contact with the eyes.

Stop use and ask a doctor

if irritation occurs or if there is no improvement within 4 weeks.

Keep out of the reach of children.

If swallowed, get medical help or contact a Poison Control Center right away.

Directions

- Wash the affected area and dry thoroughly.
- Apply a thin layer of the product over the affected area twice daily (morning and night) or as directed by a doctor.
- Supervise children in the use of this product.
- For athlete's foot: Pay special attention to spaces between the toes; wear well fitting, ventilated shoes, and change shoes and socks at least once daily.
- Use daily for 4 weeks.
- If condition persists, consults a physician.
- This product is not effective on the scalp or nails.

Inactive ingredients

Cetyl alcohol, Glycerin, Polyethylene Glycol 500, Polyethylene glycol 4000, Propylene glycol, Sodium bisulfite, Sodium laureth sulfate, water, Zinc stearate.